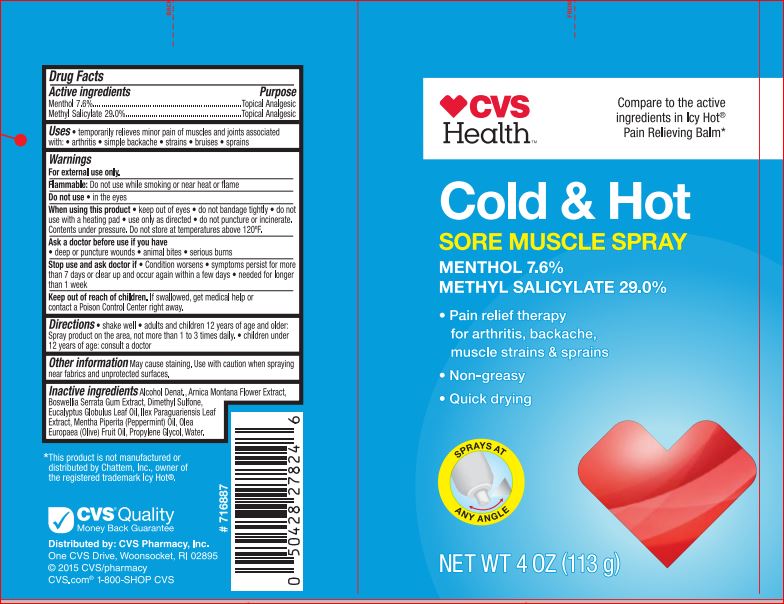 DRUG LABEL: Cold and Hot
NDC: 59779-269 | Form: SPRAY
Manufacturer: CVS
Category: otc | Type: HUMAN OTC DRUG LABEL
Date: 20180510

ACTIVE INGREDIENTS: MENTHOL 7.6 g/100 g; METHYL SALICYLATE 29.0 g/100 g
INACTIVE INGREDIENTS: ARNICA MONTANA FLOWER; INDIAN FRANKINCENSE; EUCALYPTUS OIL; DIMETHYL SULFONE; ILEX PARAGUARIENSIS LEAF; PEPPERMINT OIL; WATER; ALCOHOL; OLIVE OIL; Propylene Glycol

Active ingredients

Menthol 7.60%
Methyl Salicylate 29.00%

Purpose

Topical analgesic

Uses

For the temporary relief of minor aches and pains of muscles and
joints associated with: • arthritis • simple backache • muscle strains
• bruises • sprains

Warnings

For external use only.

Flammable • keep away from fire or flame • do not use while smoking or
near heat or flame • avoid long term storage above 104˚F. • do not puncture
or incinerate. Contents under pressure. • do not store at temperatures
above 120˚F.
When using this product • avoid contact with eyes and mucous
membranes • do not apply to wounds or damaged skin • do not bandage
tightly • use only as directed
Stop use and ask doctor if • condition worsens • symptoms persist for
more than 7 days or clear up and occur again within a few days • needed for
longer than 1 week
If pregnant or breast-feeding, ask a health professional before use.

Keep out of reach of children.

If swallowed, get help or contact a Poison Control Center right away.

Directions

• shake well • adults and children 2 years of age and older:
spray product on affected area, not more than 3 to 4 times
daily. • children under 2 years of age: consult a doctor

Inactive ingredients

Alcohol Denat.
Arnica Montana Flower Extract
Boswellia Serrata Gum Extract
Dimethyl Sulfone
Eucalyptus Globulus Leaf Oil
Ilex Paraguariensis Leaf Extract
Mentha Piperita (Peppermint) Oil
Olea Europaea (Olive) Fruit Oil
Propylene Glycol
Water